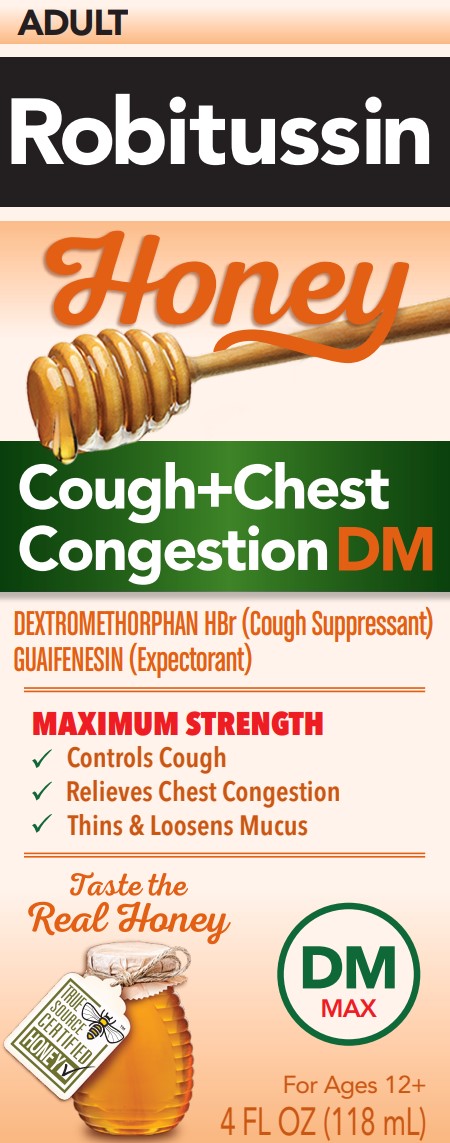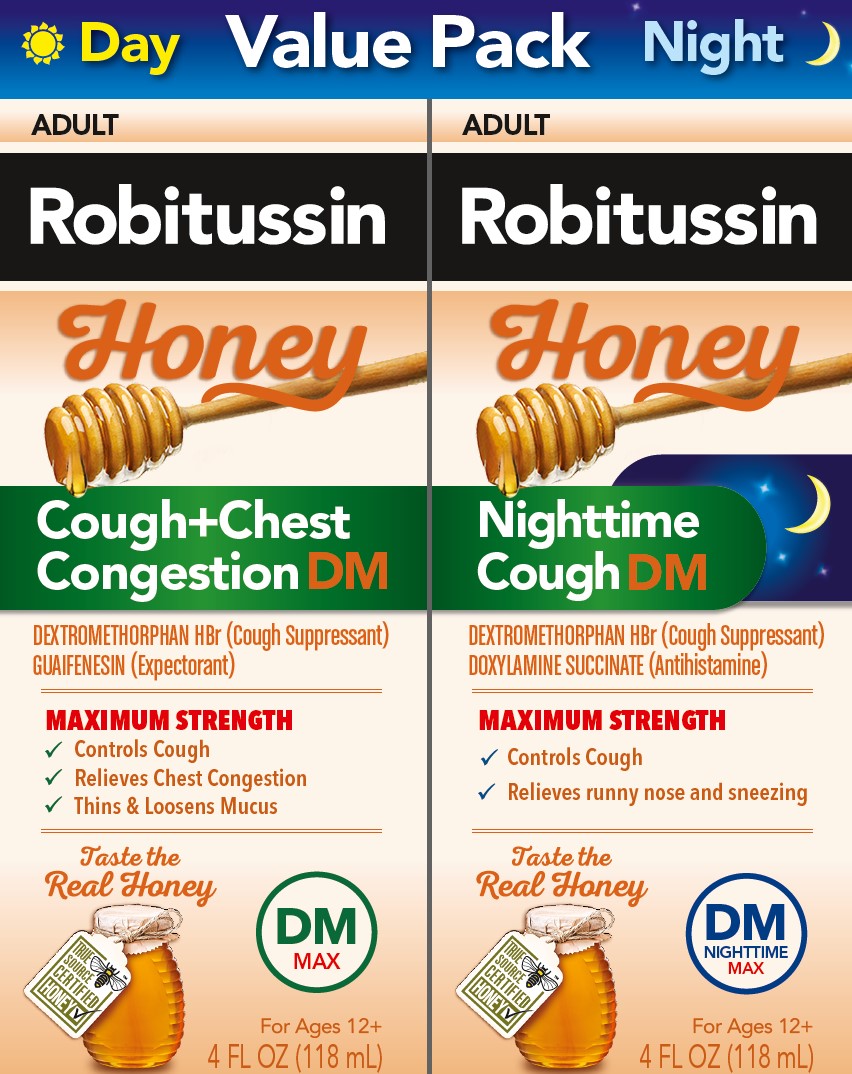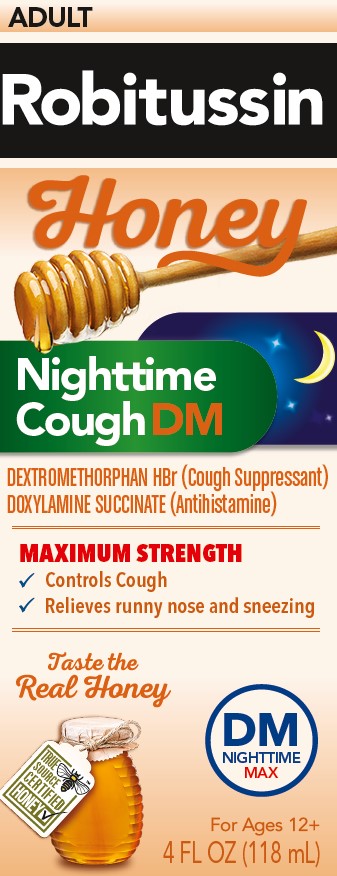 DRUG LABEL: Robitussin

NDC: 0031-2059 | Form: KIT | Route: ORAL
Manufacturer: Haleon US Holdings LLC
Category: otc | Type: HUMAN OTC DRUG LABEL
Date: 20251106

ACTIVE INGREDIENTS: DEXTROMETHORPHAN HYDROBROMIDE 20 mg/20 mL; GUAIFENESIN 400 mg/20 mL; DEXTROMETHORPHAN HYDROBROMIDE 30 mg/20 mL; DOXYLAMINE SUCCINATE 12.5 mg/20 mL
INACTIVE INGREDIENTS: ANHYDROUS CITRIC ACID; CARBOXYMETHYLCELLULOSE SODIUM, UNSPECIFIED; GLYCERIN; HONEY; POLYETHYLENE GLYCOL, UNSPECIFIED; PROPYLENE GLYCOL; WATER; SODIUM BENZOATE; SODIUM CITRATE, UNSPECIFIED FORM; SODIUM GLUCONATE; SUCRALOSE; XANTHAN GUM; ZINC GLUCONATE; ANHYDROUS CITRIC ACID; CARBOXYMETHYLCELLULOSE SODIUM, UNSPECIFIED; GLYCERIN; LACTIC ACID, UNSPECIFIED FORM; HONEY; POLYETHYLENE GLYCOL, UNSPECIFIED; PROPYLENE GLYCOL; WATER; SODIUM BENZOATE; SODIUM CITRATE, UNSPECIFIED FORM; SODIUM GLUCONATE; SUCRALOSE; XANTHAN GUM; ZINC GLUCONATE

Drug Facts

Active ingredients (in each 20 mL)– Robitussin Honey Maximum Strength Cough + Chest Congestion DM

Dextromethorphan HBr 20 mg

Guaifenesin 400 mg

Purposes– Robitussin Honey Maximum Strength Cough + Chest Congestion DM

Cough suppressant

Expectorant

Uses– Robitussin Honey Maximum Strength Cough + Chest Congestion DM

- temporarily relieves cough due to minor throat and bronchial irritation as may occur with a cold
- helps loosen phlegm (mucus) and thin bronchial secretions to drain bronchial tubes

Warnings– Robitussin Honey Maximum Strength Cough + Chest Congestion DM

Click here to enter Warnings

Do not use

if you are now taking a prescription monoamine oxidase inhibitor (MAOI) (certain drugs for depression, psychiatric, or emotional conditions, or Parkinson’s disease), or for 2 weeks after stopping the MOAI drug. If you do not know if your prescription drug contains an MAOI, ask a doctor or pharmacist before taking this product.

Ask a doctor before use if you have

- cough that occurs with too much phlegm (mucus)
- cough that lasts or is chronic such as occurs with smoking, asthma, chronic bronchitis, or emphysema

Stop use and ask a doctor if

cough lasts more than 7 days, comes back, or is accompanied by fever, rash, or persistent headache.

These could be signs of a serious condition.

If pregnant or breast-feeding,

ask a health professional before use.

Keep out of reach of children.

In case of overdose, get medical help or contact a Poison Control Center right away.

Directions– Robitussin Honey Maximum Strength Cough + Chest Congestion DM

- do not take more than 6 doses in any 24-hour period
- measure only with dosing cup provided
- keep dosing cup with product
- mL = milliliter
- this adult product is not intended for use in children under 12 years of age

age | dose
adults and children 12 years and over | 20 mL every 4 hours
children under 12 years | do not use

Other information– Robitussin Honey Maximum Strength Cough + Chest Congestion DM

- each 20 mL contains:sodium 21 mg
- store at 20-25°C (68-77°F). Do not refrigerate.

Inactive ingredients– Robitussin Honey Maximum Strength Cough + Chest Congestion DM

anhydrous citric acid, carboxymethylcellulose sodium, glycerin, natural and artificial flavors, natural grade A honey, polyethylene glycol, propylene glycol, purified water, sodium benzoate, sodium citrate, sodium gluconate, sucralose, xanthan gum, zinc gluconate

Questions or comments?– Robitussin Honey Maximum Strength Cough + Chest Congestion DM

call weekdays from 8 AM to 6 PM EST at 1-800-245-1040

Active ingredients (in each 20 mL)– Robitussin Honey Maximum Strength Nighttime Cough DM

Dextromethorphan HBr 30 mg

Doxylamine succinate 12.5 mg

Purposes– Robitussin Honey Maximum Strength Nighttime Cough DM

Cough suppressant

Antihistamine

Uses– Robitussin Honey Maximum Strength Nighttime Cough DM

- temporarily relieves cough due to minor throat and bronchial irritation as may occur with a cold
- temporarily relieves these symptoms due to hay fever or other upper respiratory allergies:
  - runny nose
  - sneezing
  - itchy, watery eyes
  - itching of the nose or throat
- controls the impulse to cough to help you sleep

Warnings– Robitussin Honey Maximum Strength Nighttime Cough DM

Click here to enter Warnings

Do not use

- to sedate a child or to make a child sleepy
- if you are now taking a prescription monoamine oxidase inhibitor (MAOI) (certain drugs for depression, psychiatric, or emotional conditions, or Parkinson’s disease), or for 2 weeks after stopping the MAOI drug. If you do not know if your prescription drug contains an MAOI, ask a doctor or pharmacist before taking this product.

Ask a doctor before use if you have

- trouble urinating due to an enlarged prostate gland
- glaucoma
- a cough that occurs with too much phlegm (mucus)
- a breathing problem or chronic cough that lasts or as occurs with smoking, asthma, chronic bronchitis or emphysema

Ask a doctor or pharmacist before use if you are

taking sedatives or tranquilizers

When using this product

- do not use more than directed
- marked drowsiness may occur
- avoid alcoholic drinks
- alcohol, sedatives, and tranquilizers may increase drowsiness
- be careful when driving a motor vehicle or operating machinery
- excitability may occur, especially in children

Stop use and ask a doctor if

cough lasts more than 7 days, comes back, or is accompanied by fever, rash, or persistent headache. These could be signs of a serious condition.

If pregnant or breast-feeding,

ask a health professional before use.

Keep out of reach of children.

In case of overdose, get medical help or contact a Poison Control Center right away.

Directions– Robitussin Honey Maximum Strength Nighttime Cough DM

- measure only with dosing cup provided
- keep dosing cup with product
- mL = milliliter
- do not take more than 4 doses in any 24-hour period
- this adult product is not intended for use in children under 12 years of age

age | dose
adults and children 12 years and over | 20 mL every 6 hours
children under 12 years | do not use

Other information– Robitussin Honey Maximum Strength Nighttime Cough DM

- each 20 mL contains:sodium 21 mg
- store at 20-25°C (68-77°F).

Inactive ingredients– Robitussin Honey Maximum Strength Nighttime Cough DM

anhydrous citric acid, blueberry juice concentrate, carboxymethylcellulose sodium, glycerin, lactic acid, natural and artificial flavors, natural grade A honey, polyethylene glycol, propylene glycol, purified water, sodium benzoate, sodium citrate, sodium gluconate, sucralose, xanthan gum, zinc gluconate

Questions or comments?– Robitussin Honey Maximum Strength Nighttime Cough DM

call weekdays from 8 AM to 6 PM EST at 1-800-245-1040

Additional Information – Robitussin Honey DM Day Night Value Pack

Packaged with Tamper-Evident bottle cap.

Do Not Use if breakable ring is separated or missing.

Do not take both products within 6 hours of each other.

ADULT

Robitussin

Honey

This dynamic duo combines the great taste of natural honey you want with the powerful, effective cough relief you need.

Made with RealHONEY

TRUE SOURCE CERTIFIED HONEY

Gluten Free

No Artificial Colors

PARENTS:Learn about teen medicine abuse

www.StopMedicineAbuse.org

Principal Display Panel – Robitussin Honey DM Day Night Value Pack

DAY NIGHT VALUE PACK

ADULT

Robitussin

Honey

Cough+Chest Congestion DM

DEXTROMETHORPHAN HBr (Cough Suppressant)

GUAIFENESIN (Expectorant)

MAXIMUM STRENGTH

- Controls Cough
- Relieves Chest Congestion
- Thins & loosens Mucus

Taste the Real Honey

DMMAX

For Ages 12+

4 FL OZ (118 mL)

ADULT

Robitussin

Honey

Nighttime Cough DM

DEXTROMETHORPHAN HBr (Cough Suppressant)

DOXYLAMINE SUCCINATE (Antihistamine)

MAXIMUM STRENGTH

- Controls Cough
- Relieves runny nose and sneezing

Taste the Real Honey

DMNIGHTTIME MAX

For Ages 12+

4 FL OZ (118 mL)

Principal Display Panel – Robitussin Honey Maximum Strength Cough + Chest Congestion DM

ADULT

Robitussin

Honey

Cough+Chest Congestion DM

DEXTROMETHORPHAN HBr (Cough Suppressant)

GUAIFENESIN (Expectorant)

MAXIMUM STRENGTH

- Controls Cough
- Relieves Chest Congestion
- Thins & loosens Mucus

Taste the Real Honey

DMMAX

For Ages 12+

4 FL OZ (118 mL)

Principal Display Panel – Robitussin Honey Maximum Strength Nighttime Cough DM

ADULT

Robitussin

Honey

Nighttime Cough DM

DEXTROMETHORPHAN HBr (Cough Suppressant)

DOXYLAMINE SUCCINATE (Antihistamine)

MAXIMUM STRENGTH

- Controls Cough
- Relieves runny nose and sneezing

Taste the Real Honey

DMNIGHTTIME MAX

For Ages 12+

4 FL OZ (118 mL)